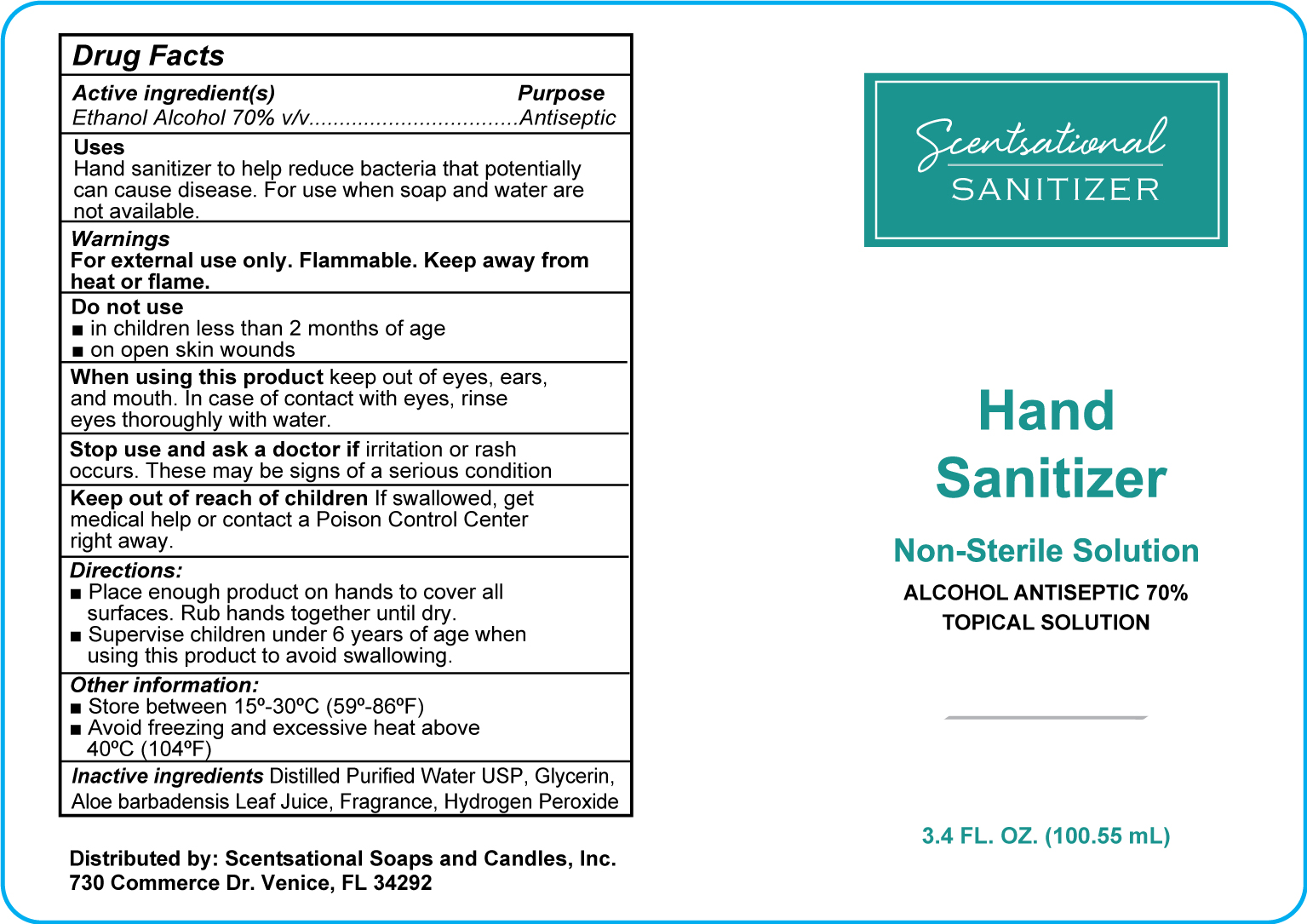 DRUG LABEL: Hand Sanitizer
NDC: 75078-004 | Form: SPRAY
Manufacturer: Scentsational Soaps & Candles, Inc.
Category: otc | Type: HUMAN OTC DRUG LABEL
Date: 20201006

ACTIVE INGREDIENTS: ALCOHOL 70 mL/100 mL
INACTIVE INGREDIENTS: WATER 26.425 mL/100 mL; GLYCERIN 1.45 mL/100 mL; HYDROGEN PEROXIDE 0.125 mL/100 mL; ALOE VERA LEAF 1 mL/100 mL

ACTIVE INGREDIENT

Alcohol 70% v/v. Purpose: Antiseptic

PURPOSE

Antiseptic, Hand Sanitizer

INDICATIONS AND USAGE

Hand Sanitizer to help reduce bacteria that potentially can cause disease. For use when soap and water are not available.

WARNINGS

For external use only. Flammable. Keep away from heat or flame.

DO NOT USE

* In children less than 2 months of age

* On open skin wounds

When using this product keep out of eyes, ears and mouth. In case of contact with eyes, rinse eyes thoroughly with water.

Stop use and ask a doctor if irritation occurs. These may be signs of a serious condition.

Keep out of reach of children. If swallowed, get medical help or contact a Poison Control Center right away.

Stop use and ask a doctor if irritation or rash occurs. This may be a sign of a serious condition.

Keep out of reach of children. If swallowed, get medical help or contact a Poison Control Center right away.

DOSAGE AND ADMINISTRATION

* Place enough product on hands to cover all surfaces. Rub hands together until dry.

* Supervise children under 6 years pf age when using this product to avoid swallowing.

STORAGE AND HANDLING

* Store between 15-30C (59-86F)

* Avoid freezing and excessive heat above 40C (104F)

INACTIVE INGREDIENT

Purified Water USP. Gycerin, Aloe barbadensis Leaf Juice, Fragrance, Hydrogen Peroxide

PACKAGE LABEL

100.55 mL NDC: 75078-004-01